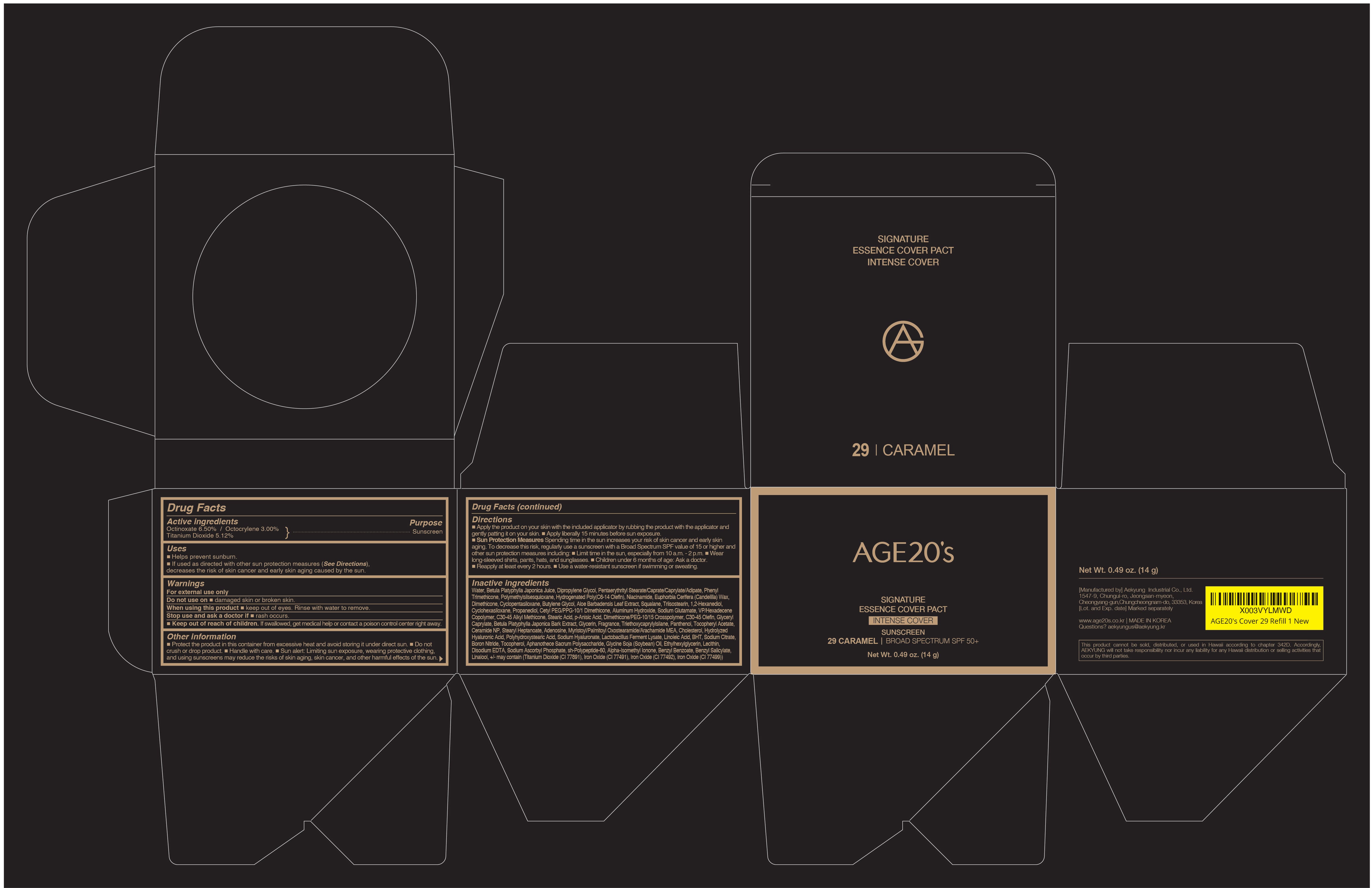 DRUG LABEL: AGE20S SIGNATURE ESSENCE COVER PACT INTENSE COVER 29 CARAMEL
NDC: 67225-5231 | Form: CREAM
Manufacturer: Aekyung Industrial Co., Ltd.
Category: otc | Type: HUMAN OTC DRUG LABEL
Date: 20251208

ACTIVE INGREDIENTS: TITANIUM DIOXIDE 0.7168 g/14 g; OCTOCRYLENE 0.42 g/14 g; OCTINOXATE 0.91 g/14 g
INACTIVE INGREDIENTS: WATER; PANTHENOL; BUTYLATED HYDROXYTOLUENE; ALOE VERA LEAF; P-ANISIC ACID; CERAMIDE NP; CYCLOMETHICONE 6; MONOSODIUM GLUTAMATE; POLYMETHYLSILSESQUIOXANE (11 MICRONS); PENTAERYTHRITYL STEARATE; HYDROGENATED POLY(C6-14 OLEFIN; 2 CST); PHENYL TRIMETHICONE; POLYHYDROXYSTEARIC ACID STEARATE; EDETATE DISODIUM; ADENOSINE; ETHYLHEXYLGLYCERIN; ALUMINUM HYDROXIDE; HYALURONIC ACID; CHOLESTEROL; C30-45 ALKYL METHICONE; BETULA PLATYPHYLLA RESIN; CANDELILLA WAX; SQUALANE; SODIUM CITRATE; CETYL PEG/PPG-10/1 DIMETHICONE (HLB 2); CYCLOMETHICONE 5; SODIUM ASCORBYL PHOSPHATE; DIPROPYLENE GLYCOL; LINOLEIC ACID; TOCOPHEROL; DIMETHICONE; BUTYLENE GLYCOL; HYDROGENATED SOYBEAN LECITHIN; TRIISOSTEARIN; FERROSOFERRIC OXIDE; 1,2-HEXANEDIOL; HYALURONATE SODIUM; STEARIC ACID; STEARYL HEPTANOATE; FERRIC OXIDE YELLOW; GLYCERIN; DIMETHICONE/PEG-10/15 CROSSPOLYMER; ALPHA-TOCOPHEROL ACETATE; MYRISTOYL/PALMITOYL OXOSTEARAMIDE/ARACHAMIDE MEA; BORON NITRIDE; GLYCERYL CAPRYLATE; NIACINAMIDE; PROPANEDIOL; FERRIC OXIDE RED; VINYLPYRROLIDONE/HEXADECENE COPOLYMER; TRIETHOXYCAPRYLYLSILANE; C30-45 OLEFIN; SOYBEAN OIL

67225-5231 AGE20S SIGNATURE ESSENCE COVER PACT INTENSE COVER 29 CARAMEL

ACTIVE INGREDIENT

Octinoxate 6.50%

Titanium Dioxide 5.12%

Octocrylene 3.00%

PURPOSE

Sunscreen

INDICATIONS AND USAGE

■ Helps prevent sunburn.

■ If used as directed with other sun protection measures (See Directions), decreases the risk of skin cancer and early skin aging caused by the sun.

WARNINGS

For external use only

DO NOT USE

■ damaged skin or broken skin

WHEN USING

this product ■ keep out of eyes. Rinse with water to remove.

STOP USE

and ask a doctor ■ rash occurs.

KEEP OUT OF REACH OF CHILDREN

If swallowed, get medical help or contact poison control cneter right away.

OTHER SAFETY INFORMATION

■ Protect the product in the container from excessive heat and avoid storing it under direct sun. ■ Do not crush or drop product. ■ Handle with care. ■ Sun alert: Limiting sun exposure. wearing protective clothing, and using sunscreens may reduce the risks of skin aging, skin cancer, and other harmful effects of the sun.

Directions
■ Apply the product on your skin with the included applicator by rubbing the product with the applicator and gently patting it on your skin.■ Apply liberally 15 minutes before sun exposure.
■ Sun Protection Measures Spending time in the sun increases your risk of skin cancer and early skin aging. To decrease this risk, regularly use a sunscreen with a Broad Spectrum SPF value of 15 or higher and other sun protection measures including: Limit time in the sun, especially from 10a.m. - 2 p.m. ■ Wear long-sleeved shirts, pants, hats, and sunglasses. Children under 6 months of age: Ask a doctor. ■ Reapply at least every 2 hours.■ Use a water-resistant sunscreen if swimming or sweating.

INACTIVE INGREDIENT

Water, Betula Platyphylla Japonica Juice, Dipropylene Glycol, Pentaerythrityl Stearate/Caprate/Caprylate/Adipate, Phenyl Trimethicone, Polymethylsilsesquioxane, Hydrogenated Poly(C6-14 Olefin), Niacinamide, Euphorbia Cerifera (Candelilla) Wax, Dimethicone, Cyclopentasiloxane, Butylene Glycol, Aloe Barbadensis Leaf Extract, Squalane, Triisostearin, 1,2-Hexanediol, Cyclohexasiloxane, Propanediol, Cetyl PEG/PPG-10/1 Dimethicone, Aluminum Hydroxide, Sodium Glutamate, VP/Hexadecene Copolymer, C30-45 Alkyl Methicone, Stearic Acid, p-Anisic Acid, Dimethicone/PEG-10/15 Crosspolymer, C30-45 Olefin, Glyceryl Caprylate, Betula Platyphylla Japonica Bark Extract, Glycerin, Fragrance, Triethoxycaprylylsilane, Panthenol, Tocopheryl Acetate, Ceramide NP, Stearyl Heptanoate, Adenosine, Myristoyl/Palmitoyl Oxostearamide/Arachamide MEA, Cholesterol, Hydrolyzed Hyaluronic Acid, Polyhydroxystearic Acid, Sodium Hyaluronate, Lactobacillus Ferment Lysate, Linoleic Acid, BHT, Sodium Citrate, Boron Nitride, Tocopherol, Aphanothece Sacrum Polysaccharide, Glycine Soja (Soybean) Oil, Ethylhexylglycerin, Lecithin, Disodium EDTA, Sodium Ascorbyl Phosphate, sh-Polypeptide-60, Alpha-Isomethyl Ionone, Benzyl Benzoate, Benzyl Salicylate, Linalool, +/- may contain (Titanium Dioxide (CI 77891), Iron Oxide (CI 77491), Iron Oxide (CI 77492), Iron Oxide (CI 77499))